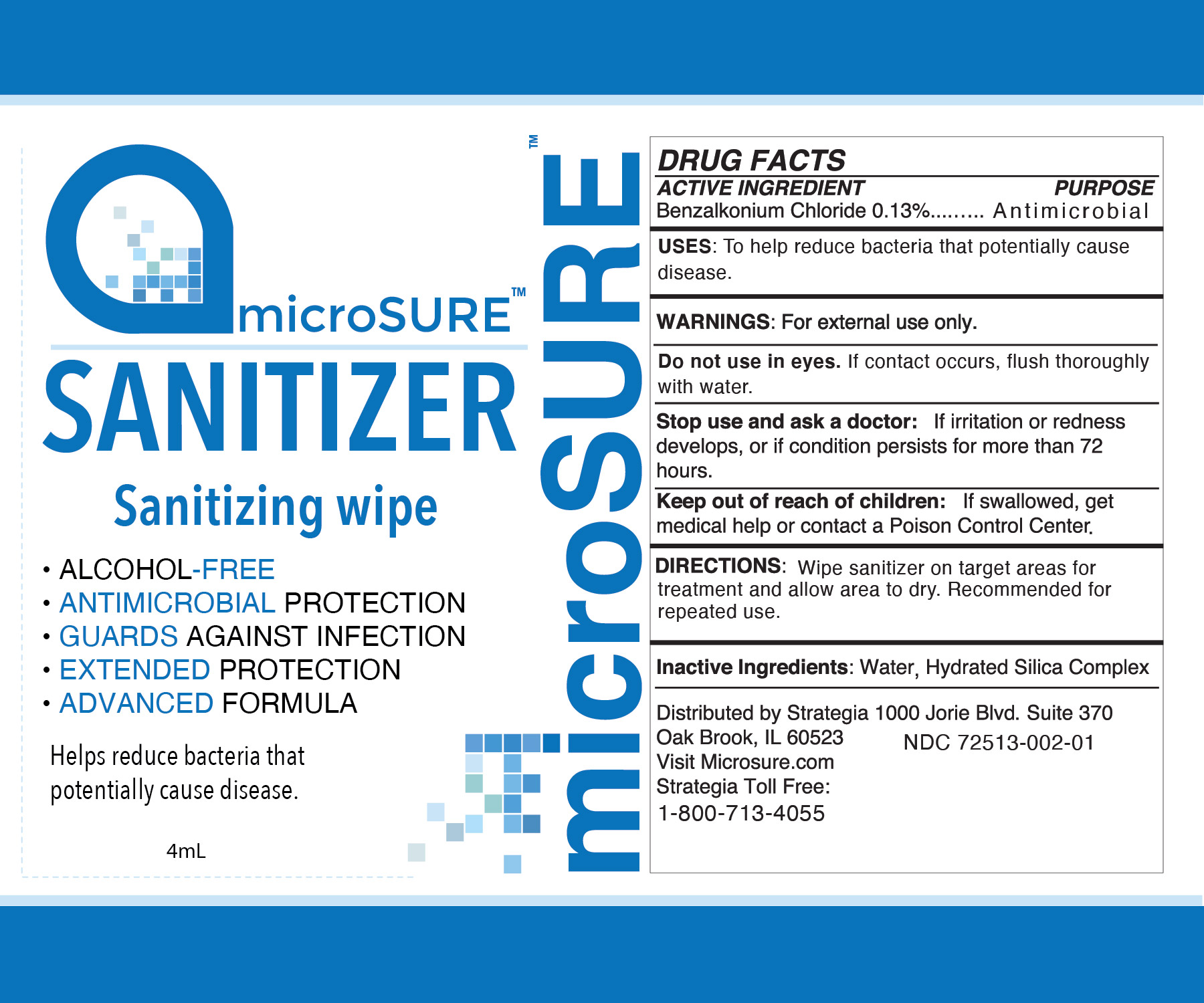 DRUG LABEL: Microsure Sanitizer
NDC: 72513-002 | Form: CLOTH
Manufacturer: Strategia Project Management, Inc.
Category: otc | Type: HUMAN OTC DRUG LABEL
Date: 20210129

ACTIVE INGREDIENTS: BENZALKONIUM CHLORIDE 0.13 g/100 mL
INACTIVE INGREDIENTS: HYDRATED SILICA 0.04 g/100 mL; WATER 99.83 g/100 mL

Microsure Sanitizer

ACTIVE INGREDIENT

Benzalkonium Chloride 0.13%

PURPOSE

Antimicrobial

USES:

To help reduce bacteria that potentially cause disease.

WARNINGS:

For external use only.

Do not use

in eyes. If contact occurs, flush thoroughly with water.

Stop use and ask a doctor:

If irritation or redness develops, or if condition persists for more than 72 hours.

Keep out of reach of children:

If swallowed, get medical help or contact a Poison Control Center.

DIRECTIONS:

Wipe sanitizer on target areas for treatment and allow area to dry. Recommended for repeated use.

Inactive Ingredients:

Water, Hydrated Silica Complex